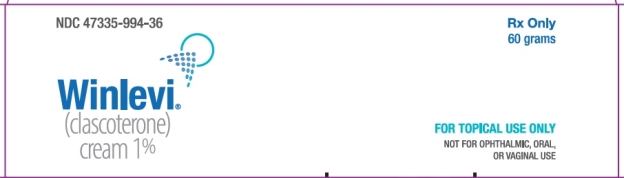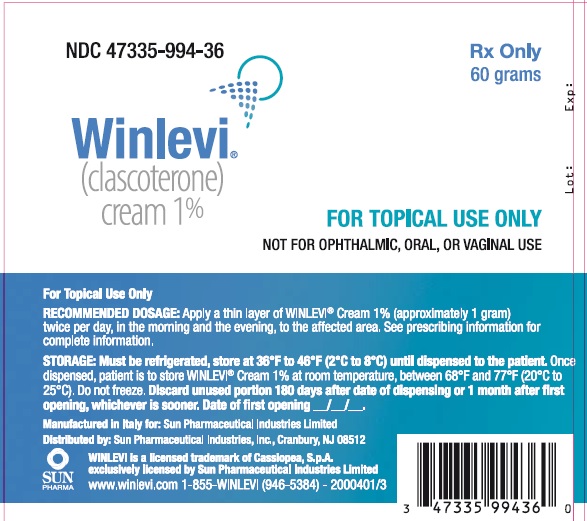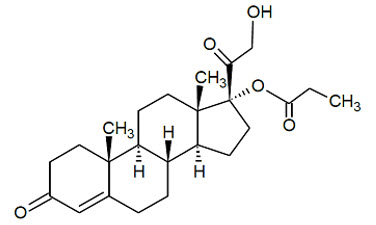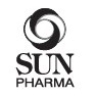 DRUG LABEL: Winlevi
NDC: 47335-994 | Form: CREAM
Manufacturer: Sun Pharmaceutical Industries, Inc.
Category: prescription | Type: HUMAN PRESCRIPTION DRUG LABEL
Date: 20250102

ACTIVE INGREDIENTS: CLASCOTERONE 1 g/100 g
INACTIVE INGREDIENTS: PROPYLENE GLYCOL 25 g/100 g; WATER; GLYCERYL MONO- AND DICAPRYLOCAPRATE; MINERAL OIL; CETYL ALCOHOL; POLYSORBATE 80; EDETATE DISODIUM; ALPHA-TOCOPHEROL

HIGHLIGHTS OF PRESCRIBING INFORMATION

These highlights do not include all the information needed to use WINLEVI Cream safely and effectively. See full prescribing information for WINLEVI Cream.
WINLEVI®(clascoterone) cream, for topical use
Initial U.S. Approval: 2020

1 INDICATIONS AND USAGE

WINLEVI (clascoterone) cream is an androgen receptor inhibitor indicated for the topical treatment of acne vulgaris in patients 12 years of age and older. (1)

2 DOSAGE AND ADMINISTRATION

- Apply a thin layer (approximately 1 gram) to affected area twice daily (morning and evening). Avoid contact with eyes, mouth, and mucous membranes. (2)
- Not for ophthalmic, oral or vaginal use. (2)

3 DOSAGE FORM AND STRENGTHS

Cream 1%. (3)

4 CONTRAINDICATIONS

None (4)

5 WARNINGS AND PRECAUTIONS

- Local Irritation: Pruritus, burning, skin redness or peeling may be experienced with WINLEVI cream. If these effects occur, discontinue or reduce the frequency of application of WINLEVI cream. (5.1)
- Hypothalamic-pituitary-adrenal (HPA) axis suppression may occur during or after treatment with clascoterone. (5.2)
- Attempt to withdraw use if HPA axis suppression develops. (5.2)
- Pediatric patients may be more susceptible to systemic toxicity. (5.2, 8.4)
- Hyperkalemia: Elevated potassium levels were observed in some subjects during the clinical trials. (12.2)

6 ADVERSE REACTIONS

Most common adverse reactions occurring in 7 to 12% of patients are erythema/reddening, pruritus and scaling/dryness. Additionally, edema, stinging, and burning occurred in >3% of patients and were reported in a similar percentage of subjects treated with vehicle. (6.1)

To report SUSPECTED ADVERSE REACTIONS, contact Sun Pharmaceutical Industries, Inc. 1-800-818-4555 or FDA at 1-800-FDA-1088 or http://www.fda.gov/medwatch.

FULL PRESCRIBING INFORMATION

1 INDICATIONS AND USAGE

WINLEVI (clascoterone) cream is an androgen receptor inhibitor indicated for the topical treatment of acne vulgaris in patients 12 years of age and older.

2 DOSAGE AND ADMINISTRATION

Cleanse the affected area gently. After the skin is dry, apply a thin uniform layer of WINLEVI cream twice per day, in the morning and the evening, to the affected area. Avoid accidental transfer of WINLEVI cream into eyes, mouth or other mucous membranes. If contact with mucous membranes occurs, rinse thoroughly with water.

WINLEVI cream is for topical use only. WINLEVI cream is not for ophthalmic, oral or vaginal use.

3 DOSAGE FORM AND STRENGTHS

Cream 1%. Each gram of WINLEVI cream contains 10 mg of clascoterone in a white to almost white cream.

4 CONTRAINDICATIONS

None.

5 WARNINGS AND PRECAUTIONS

5.1 Local Skin Reactions

WINLEVI cream may induce local irritation (erythema/redness, pruritus, scaling/ dryness). Concomitant use with other potentially irritating topical products (medicated or abrasive soaps and cleansers, soaps and cosmetics that have a strong drying effect and products with high concentrations of alcohol, astringents, spices or lime) should be limited.

The product should not be applied to cuts, abrasions, eczematous or sunburned skin.

5.2 Hypothalamic-pituitary-adrenal (HPA) Axis Suppression

Hypothalamic-pituitary-adrenal (HPA) axis suppression was observed and may occur during or after treatment with clascoterone. In the PK trial, all subjects returned to normal HPA axis function at follow-up 4 weeks after stopping treatment [see Clinical Pharmacology (12.2)]. Conditions which augment systemic absorption include use over large surface areas, prolonged use, and the use of occlusive dressings.

If HPA axis suppression develops, an attempt should be made to withdraw the drug.

Pediatric patients may be more susceptible to systemic toxicity.

6 ADVERSE REACTIONS

6.1 Clinical Trials Experience

Because clinical trials are conducted under widely varying conditions, adverse reaction rates observed in the clinical trials of a drug cannot be directly compared to rates in the clinical trials of another drug and may not reflect the rates observed in practice.

In two identical multicenter, randomized, double-blind, vehicle-controlled trials, 1421 subjects 12 years and older with facial acne vulgaris applied WINLEVI cream or vehicle twice daily for 12 weeks. Overall, 62% of the subjects were female, and 38% were male, 91% of the patients were Caucasian, and the mean age was 19.7 years.

Local skin reactions (edema, erythema/redness, pruritus, scaling/dryness, skin atrophy, stinging/burning, striae rubrea, telangiectasia) were observed during the 12-week treatment and occurred in a similar percentage of subjects treated with vehicle. Local skin reactions reported by ≥ 1% of subjects treated with WINLEVI cream are shown in the following table.

Table 1. Incidence of New or Worsening Local Skin Reactions Reported by ≥ 1% of Subjects Treated with WINLEVI Cream After Day 1 in 12-Week Controlled Clinical Trials

 | WINLEVI Cream 1% (N=674a) | Vehicle Cream (N=656a)
Edema | 24 (3.6%) | 23 (3.5%)
Erythema/redness | 82 (12.2%) | 101 (15.4%)
Pruritus | 52 (7.7%) | 54 (8.2%)
Scaling/dryness | 71 (10.5%) | 68 (10.4%)
Skin atrophy | 11 (1.6%) | 17 (2.6%)
Stinging/burning | 28 (4.2%) | 28 (4.3%)
Striae rubrae | 17 (2.5%) | 10 (1.5%)
Telangiectasia | 8 (1.2%) | 12 (1.8%)
aThe denominators for calculating the percentages were the 674 of 709 subjects treated with WINLEVI cream and 656 of 712 subjects treated with vehicle in these trials who had local skin reaction results reported after Day 1.

The following adverse reactions associated with the use of WINLEVI cream were identified in clinical trials and long-term safety studies.

Metabolism: hyperkalemia [see Clinical Pharmacology (12.2)]

Reproductive: polycystic ovaries, amenorrhea.

8 USE IN SPECIFIC POPULATIONS

8.1 Pregnancy

Risk Summary

There are no available data on WINLEVI cream use in pregnant women to evaluate for a drug-associated risk of major birth defects, miscarriage, or adverse maternal or fetal outcomes. In animal reproduction studies, subcutaneous administration of clascoterone to pregnant rats and rabbits during organogenesis at doses 8 or 39 times the maximum recommended human dose (MRHD), respectively, increased malformations in rats and post-implantation loss and resorptions in rabbits (see Data).

The background risk of major birth defects and miscarriage for the indicated population is unknown. Adverse outcomes in pregnancy occur regardless of the health of the mother or the use of medications. In the U.S. general population, the estimated background risk of major birth defects and miscarriage in clinically recognized pregnancies is 2% to 4% and 15% to 20%, respectively.

Data

Animal Data

In an embryofetal development study, clascoterone was administered subcutaneously to pregnant rats at doses of 1, 5, or 25 mg/kg/day during the period of organogenesis. No clascoterone-related maternal toxicity or effects on uterine parameters were noted at doses up to 25 mg/kg/day (336 times the MRHD based on AUC comparison). Clascoterone-related malformations were noted at all dose levels, without a dose relationship. Omphalocele was noted in a single fetus at each dose level. External and visceral malformations (severe dilation of the lateral and third cerebral ventricles; thin skin, small size, and protruding tongue) were noted in two additional fetuses at 1 mg/kg/day (8 times the MRHD based on AUC comparison).

In an embryofetal development study, clascoterone was administered subcutaneously to pregnant rabbits at doses of 0.1, 0.4, or 1.5 mg/kg/day during the period of organogenesis. Post-implantation loss and resorptions were increased at 1.5 mg/kg/day (39 times the MRHD based on AUC comparison). No developmental toxicity was noted at doses up to 0.4 mg/kg/day (12 times the MRHD based on AUC comparison). No clascoterone-related maternal toxicity or fetal malformations were noted at doses up to 1.5 mg/kg/day (39 times the MRHD based on AUC comparison).

In a prenatal and postnatal development study, clascoterone was administered subcutaneously to pregnant rats at doses of 0.5, 2.5, and 12.5 mg/kg/day beginning on gestation day 6 and continuing through lactation day 20. No significant maternal or developmental toxicity was observed at doses up to 12.5 mg/kg/day (163 times the MRHD based on AUC comparison).

8.2 Lactation

Risk Summary

There are no data regarding the presence of clascoterone or metabolite in human milk, the effects on the breastfed infant or the effects on milk production. The lack of clinical data during lactation precludes a clear determination of the risk of clascoterone to an infant during lactation; therefore, the developmental and health benefits of breastfeeding should be considered along with the mother's clinical need for clascoterone and any potential adverse effects on the breastfed child from clascoterone or from the underlying maternal condition.

8.4 Pediatric Use

Safety and effectiveness of WINLEVI cream for the topical treatment of acne vulgaris have been established in 641 pediatric patients, aged 12 to 18 years in two identical multicenter, randomized, double-blind, vehicle-controlled, 12-week trials and 2 open-label pharmacokinetic studies [see Clinical Studies (14)].

Safety and effectiveness of WINLEVI cream for the topical treatment of acne vulgaris has not been established in pediatric patients under 12 years of age.

Hypothalamic-pituitary-adrenal (HPA) axis suppression was observed in 2/22 (9%) adolescent subjects. All subjects returned to normal HPA axis function at follow-up 4 weeks after stopping the treatment [see Clinical Pharmacology (12.2)].Children may be more susceptible to systemic toxicity when treated with clascoterone [see Pharmacodynamics (12.2)].

8.5 Geriatric Use

Clinical studies of WINLEVI cream did not include sufficient numbers of subjects aged 65 years of age and over to determine whether they respond differently from younger subjects. Other reported clinical experience has not identified differences in responses between the elderly and younger patients. In general, dose selection for an elderly patient should be cautious, usually starting at the low end of the dosing range, reflecting the greater frequency of decreased hepatic, renal, or cardiac function, and of concomitant disease or other drug therapy.

11 DESCRIPTION

WINLEVI (clascoterone) cream contains clascoterone, an androgen receptor inhibitor, in a cream base for topical dermatologic use. WINLEVI cream is a white to almost white cream.

Chemically, clascoterone is cortexolone-17α propionate. Clascoterone is a white to almost white powder, practically insoluble in water. The compound has the empirical formula C24H34O5and molecular weight of 402.5 g/mol. The structural formula is shown below.

Each gram of WINLEVI cream 1% contains 10 mg of clascoterone in a cream base of cetyl alcohol, citric acid monohydrate, edetate disodium, mineral oil, mono- and di-glycerides, polysorbate 80, propylene glycol, purified water, and vitamin E.

12 CLINICAL PHARMACOLOGY

12.1 Mechanism of Action

Clascoterone is an androgen receptor inhibitor. The mechanism of action of WINLEVI cream for the topical treatment of acne vulgaris is unknown.

12.2 Pharmacodynamics

Hypothalamic-Pituitary-Adrenal (HPA) Axis Suppression

HPA axis suppression was evaluated in adult (n=20) and adolescent (n=22) subjects with acne vulgaris following twice daily application of WINLEVI cream for 2 weeks in the pharmacokinetic study described in Section 12.3. HPA axis suppression indicated by 30-minute post-stimulation serum cortisol level of ≤18 mcg/dL was observed in 1/20 (5%) of adult subjects and 2/22 (9%) of adolescent subjects at Day 14. All subjects returned to normal HPA axis function at follow-up 4 weeks after the end of treatment.

Potassium

Shifts from normal to elevated potassium levels were observed in 5% of clascoterone-treated subjects and 4% of vehicle-treated subjects.

Cardiac Electrophysiology

At approximately 2-times the systemic exposure observed with the maximum dose, WINLEVI cream does not prolong the QT interval to any clinically relevant extent.

12.3 Pharmacokinetics

Absorption

Following topical treatment of WINLEVI cream for 2 weeks with a mean dose of approximately 6 grams applied twice daily to adult subjects with moderate to severe acne vulgaris (n=20), systemic concentrations of clascoterone were at steady state by Day 5. On Day 14, the mean ± SD maximum plasma concentration (Cmax) was 4.5 ± 2.9 ng/mL, the mean ± SD area under the plasma concentration-time over the dosing interval (AUCꞇ) was 37.1 ± 22.3 h*ng/mL and the mean ± SD average plasma concentration (Cavg) was 3.1 ± 1.9 ng/mL.

Distribution

Plasma protein binding of clascoterone is 84% to 89% and is independent of concentrations, in vitro.

Elimination

Metabolism

Following topical treatment with WINLEVI cream, the plasma concentrations of cortexolone, a possible primary metabolite of clascoterone, were detectable and generally below or near the lower limit of quantitation (0.5 ng/mL) in subjects ≥12 years of age with acne vulgaris.

The in vitro study indicated that incubation of 10 µmol/L clascoterone with human cryopreserved hepatocytes generated cortexolone as the possible primary metabolite and other unidentified metabolites, including conjugated metabolites.

Excretion

Excretion of clascoterone has not been fully characterized in humans.

Specific Populations

Pediatric Patients

In adolescent subjects ≥ 12 to <18 years of age (n=22) after 2 weeks of twice daily treatment with mean dose of approximately 6 grams of WINLEVI cream (or mean dose of approximately 4 grams in younger, smaller subjects), steady-state concentrations of clascoterone were achieved by Day 5. Clascoterone systemic exposure in adolescents was similar to those observed in adults.

Drug Interaction Studies

Clinical Studies

No clinical studies evaluating the drug interaction potential of WINLEVI cream have been conducted.

In Vitro Studies

CYP Enzymes:Clascoterone inhibited CYP 1A2, 2B6, 2C8, 2C9, 2C19, 2D6, 2E1, or 3A4 with an IC50value of >40 µM. Clascoterone up to 30 µM did not induce CYP 1A2, 2B6, or 3A4. These findings suggest that WINLEVI cream has no clinically meaningful effect on the PK of drugs metabolized by CYP 1A2, 2B6, 2C8, 2C9, 2C19, 2D6, 2E1, or 3A4.

13 NONCLINICAL TOXICOLOGY

13.1 Carcinogenesis, Mutagenesis, Impairment of Fertility

Clascoterone cream (0.1%, 1%, or 5%) was not carcinogenic after daily topical administration in a 2-year carcinogenicity study in rats. An increased incidence of the non-neoplastic finding of atrophy of the skin and subcutis at the application site was reported in males and females treated with 1% and 5% clascoterone cream.

Clascoterone was not mutagenic in the Ames reverse mutation assay and was not clastogenic in the in vitro human lymphocyte chromosomal aberration assay. In rats, clascoterone administered via subcutaneous injection did not induce micronuclei in the bone marrow at 500 or 1000 mg/kg but a slight increase in micronuclei occurred in 2 of 5 rats at 2000 mg/kg. The response was considered equivocal. Overall, the weight of evidence indicates that clascoterone does not represent a genotoxic risk.

In a fertility and early embryonic development study in rats, clascoterone was administered subcutaneously at doses of 0.5, 2.5, or 12.5 mg/kg/day from 2 – 4 weeks before mating through mating. Clascoterone increased pre-implantation loss at 12.5 mg/kg/day (163 times the MRHD based on AUC comparison). Clascoterone had no effects on mating or fertility in rats at doses up to 12.5 mg/kg/day (163 times the MRHD based on AUC comparison). No effects were noted on development at doses up to 2.5 mg/kg/day (33 times the MRHD based on AUC comparison).

14 CLINICAL STUDIES

The safety and efficacy of WINLEVI cream 1% applied twice daily for 12 weeks for the treatment of acne vulgaris were assessed in two identically-designed, multicenter, randomized, double-blind, vehicle-controlled clinical trials (Trial 1 [NCT02608450] and Trial 2 [NCT02608476]) enrolling 1440 subjects with facial acne vulgaris. The trials enrolled subjects 9 years or older with Investigator's Global Assessment (IGA) of moderate or severe facial acne vulgaris (score of 3 or 4), 30 to 75 inflammatory lesions (papules, pustules and nodules), and 30 to 100 non-inflammatory lesions (open and closed comedones).

A total of 1421 subjects 12 years and older with facial acne vulgaris were enrolled. Of these subjects, 641 (45%) were 12 to 17 years of age, and 780 (55%) were 18 years of age or older. In addition, 62% of the subjects were female, and 91% were Caucasian. At baseline, subjects had a mean inflammatory lesion count of 42.4 and a mean non-inflammatory lesion count of 61.4. Additionally, approximately 83% of subjects had an IGA score of 3 ("moderate").

Efficacy was assessed at Week 12 by the proportion of subjects in each treatment group with at least a 2-point reduction in IGA compared to baseline and an IGA score of 0 (clear) or 1 (almost clear), absolute change and percent change from baseline in non-inflammatory and inflammatory lesions. The IGA success rate and mean absolute and percent reduction from baseline in acne lesion counts after 12 weeks of treatment for subjects 12 years of age and older are presented in the following table.

Table 2. Clinical Efficacy of WINLEVI Cream 1% in Subjects with Acne Vulgaris at Week 12

 | Trial 1 |  | Trial 2
 | WINLEVI Cream 1% N=342 | Vehicle Cream N=350 | WINLEVI Cream 1% N=367 | Vehicle Cream N=362
IGA Successa | 18.8% | 8.7% | 20.9% | 6.6%
Difference from Vehicle (95% CI) | 10.1% (4.1%, 16.0%) |  | 14.3% (8.9%, 19.7%)
Non-inflammatory Lesions
Mean Absolute Reduction | 20.4 | 13.0 | 19.5 | 10.8
Difference from Vehicle (95% CI) | 7.3 (3.5, 11.1) |  | 8.7 (4.5, 12.4)
Mean Percent Reduction | 32.6% | 21.8% | 29.6% | 15.7%
Difference from Vehicle (95% CI) | 10.8% (3.9%, 17.6%) |  | 13.8% (7.5%, 20.1%)
Inflammatory Lesions
Mean Absolute Reduction | 19.3 | 15.4 | 20.1 | 12.6
Difference from Vehicle (95% CI) | 3.9 (1.3, 6.5) |  | 7.5 (5.2, 9.9)
Mean Percent Reduction | 44.6% | 36.3% | 47.1% | 29.7%
Difference from Vehicle (95% CI) | 8.3% (2.2%, 14.4%) |  | 17.5% (11.8%, 23.1%)
aInvestigator Global Assessment (IGA) success was defined as at least a 2-point reduction in IGA compared to baseline and an IGA score of 0 (clear) or 1 (almost clear).

16 HOW SUPPLIED/STORAGE AND HANDLING

WINLEVI cream 1% is supplied in an epoxy-lined aluminum blind-end tube with a polypropylene cap closure:

NDC 47335-994-36 | 60-gram tube

STORAGE AND HANDLING

Prior to Dispensing:Store the product in a refrigerator between 36°F and 46°F (2°C and 8°C). Do not freeze.

STORAGE AND HANDLING

Dispensing Instructions for the Pharmacist:Direct the patient to store the product while in use at room temperature, between 68°F and 77°F (20°C to 25°C). Do not freeze. Discard the unused product 180 days after the date of dispensing or 1 month after first opening, whichever is sooner.

17 PATIENT COUNSELING INFORMATION

- Advise the patient to read the FDA-approved patient labeling (Patient Information).
- Avoid applying WINLEVI Cream to damaged skin (such as cuts, abrasions), eczematous areas, and sunburned skin.
- Avoid concomitant use of other potentially irritating topical products (medicated or not).

Manufactured in Italy for:

Sun Pharmaceutical Industries Limited

Distributed by:

Sun Pharmaceutical Industries, Inc.,

Cranbury, NJ 08512

Patient Information
WINLEVI (Win-levē)
(clascoterone) cream

Important Information:WINLEVI cream is for use on the skin only (topical). Do not use WINLEVI cream in or on your eyes, mouth, or vagina.

What is WINLEVI cream?
WINLEVI cream is a prescription medicine used on the skin (topical) to treat acne vulgaris in people 12 years of age and older.
It is not known if WINLEVI cream is safe and effective in children under 12 years of age.

- Before using WINLEVI cream, tell your healthcare provider about all of your medical conditions, including if you:
- have skin problems, including eczema, cuts or sunburn
- are pregnant or plan to become pregnant. It is not known if WINLEVI cream will harm your unborn baby.
- are breastfeeding or plan to breastfeed. It is not known if WINLEVI cream passes into your breast milk. Talk to your healthcare provider about the best way to feed your baby during treatment with WINLEVI cream.

Tell your healthcare provider about the medicines you take,including prescription and over-the-counter medicines, vitamins, and herbal supplements.

How should I use WINLEVI cream?

- Use WINLEVI cream exactly as your healthcare provider tells you to use it.
- Before applying WINLEVI cream, gently wash and dry the affected skin area.
- After the skin is dry, apply a thin even layer of WINLEVI cream to the affected areas 2 times each day, in the morning and the evening.
- Wash your hands after applying WINLEVI cream.

What should I avoid while using WINLEVI cream?

- Avoid using WINLEVI cream on skin areas with cuts, abrasions, eczema, or on sunburned skin.
- Avoid getting WINLEVI cream into your eyes, lips, mouth, corners of the nose, or mucous membranes. If contact with mucous membranes happens, rinse well with water.
- Avoid using skin products that may dry or irritate your skin such as:
  - medicated or abrasive soaps and cleansers
  - soaps, cleansers, and cosmetics that have strong skin drying effects
  - products that contain high amounts of alcohol
  - astringents, spices, or lime

What are the possible side effects of WINLEVI cream?
WINLEVI cream can cause serious side effects, including:

- Local skin reactions.WINLEVI cream may cause local skin irritation including itching, burning, skin redness or peeling.
- Symptoms of a disorder where the adrenal gland does not make enough of certain hormones (adrenal insufficiency) during treatment with WINLEVI.Your healthcare provider may stop your treatment with WINLEVI if you develop any adrenal problems.

The most common side effects of WINLEVI creaminclude reddening, scaling or dryness, and itching of the skin being treated.
These are not all of the possible side effects of WINLEVI cream.
Call your healthcare provider for medical advice about side effects. You may report side effects to FDA at 1-800-FDA-1088.
You may also report side effects to Sun Pharmaceutical Industries, Inc. by calling 1-800-818-4555.

How should I store WINLEVI cream?

- Store WINLEVI cream at room temperature between 68°F and 77°F (20°C to 25°C). Do not freeze.
- Throw away (discard) the unused portion 180 days after the date of dispensing or 1 month after first opening, whichever is sooner.

Keep WINLEVI cream and all medicines out of the reach of children.

General Information about the safe and effective use of WINLEVI cream.
Medicines are sometimes prescribed for purposes other than those listed in a Patient Information leaflet. Do not use WINLEVI cream for a condition for which it was not prescribed. Do not give WINLEVI cream to other people, even if they have the same symptoms you have. It may harm them. You can ask your healthcare provider or pharmacist for information about WINLEVI cream that is written for health professionals.

What are the ingredients in WINLEVI cream?
Active ingredient:clascoterone
Inactive ingredients:cetyl alcohol, citric acid monohydrate, edetate disodium, mineral oil, mono- and di-glycerides, polysorbate 80, propylene glycol, purified water, and vitamin E.

Manufactured in Italy for: Sun Pharmaceutical Industries Limited

Distributed by: Sun Pharmaceutical Industries, Inc., Cranbury, NJ 08512

WINLEVI is a licensed trademark of Cassiopea, S.p.A. exclusively licensed by Sun Pharmaceutical Industries, Ltd.

US Patents: https://www.cassiopea.com/patents

©2022 Sun Pharmaceutical Industries Limited, All right reserved.

This Patient Information has been approved by the U.S. Food and Drug Administration

Issued: 07/2022

2000405-3

PACKAGE LABEL

NDC 47335-994-36

Rx Only

WINLEVI ®

Clascoterone cream 1%

For Topical Use Only